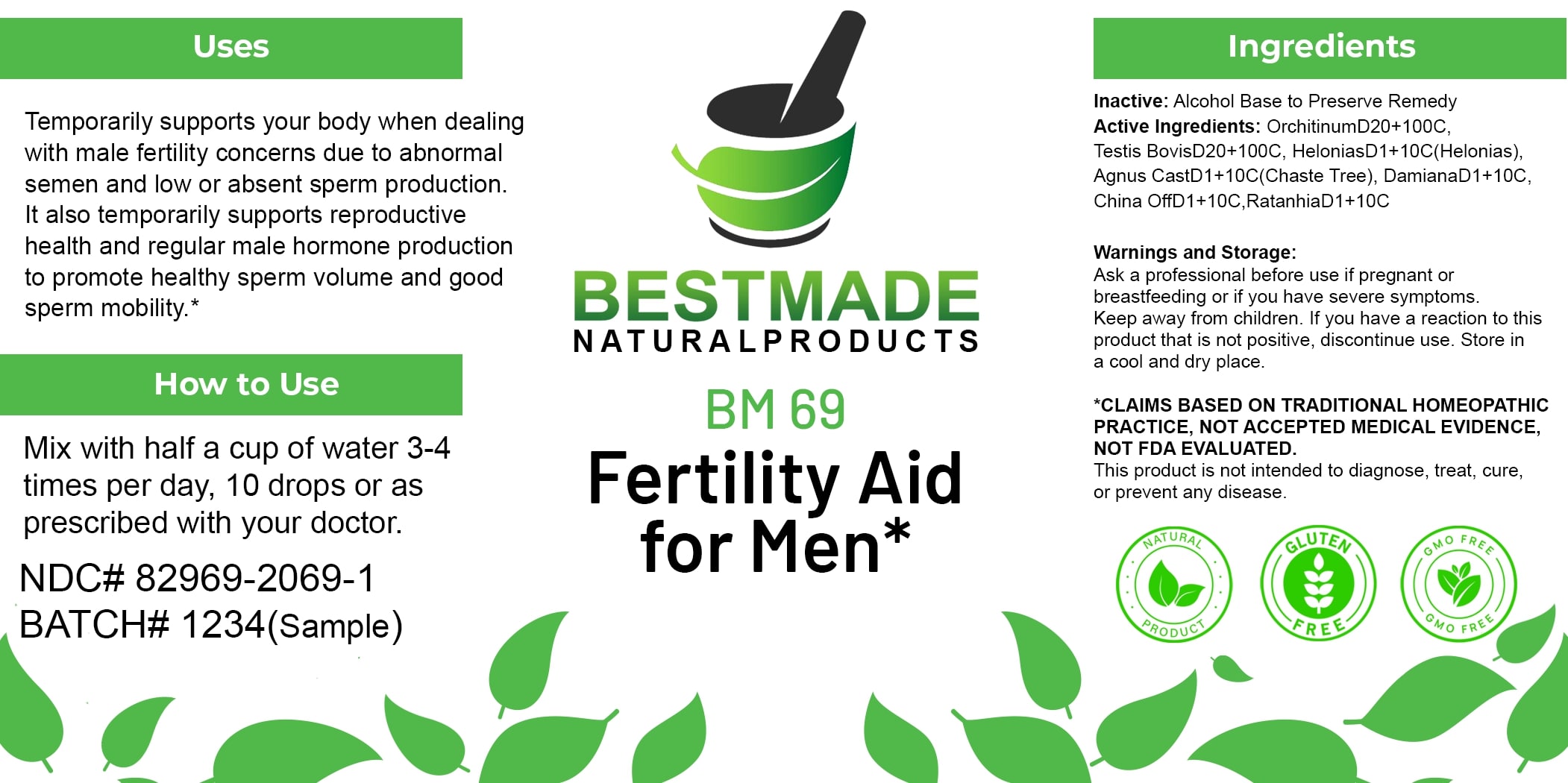 DRUG LABEL: Bestmade Natural Products BM69
NDC: 82969-2069 | Form: LIQUID
Manufacturer: Bestmade Natural Products
Category: homeopathic | Type: HUMAN OTC DRUG LABEL
Date: 20250130

ACTIVE INGREDIENTS: SUS SCROFA TESTICLE 30 [hp_C]/30 [hp_C]; TURNERA DIFFUSA LEAFY TWIG 30 [hp_C]/30 [hp_C]; KRAMERIA LAPPACEA ROOT 30 [hp_C]/30 [hp_C]; CHASTE TREE 30 [hp_C]/30 [hp_C]; BOS TAURUS TESTICLE 30 [hp_C]/30 [hp_C]; CHAMAELIRIUM LUTEUM ROOT 30 [hp_C]/30 [hp_C]; CINCHONA OFFICINALIS BARK 30 [hp_C]/30 [hp_C]
INACTIVE INGREDIENTS: ALCOHOL 30 [hp_C]/30 [hp_C]

BM69

DOSAGE AND ADMINISTRATION

How to Use

Mix with half a cup of water 3-4 times per day, 10 drops or as prescribed with your doctor.

INACTIVE INGREDIENT

Ingredients

Inactive: Alcohol Base to Preserve Remedy

ACTIVE INGREDIENT

Active Ingredients: OrchitinumD20+100C, Testis BovisD20+100C, HeloniasD1+10C(Helonias), Agnus CastD1+10C(Chaste Tree), DamianaD1+10C, China OffD1+10C, RatanhiaD1+10C

Uses

Temporarily supports your body when dealing with male fertility concerns due to abnormal semen and low or absent sperm production. It also temporarily supports reproductive health and regular male hormone production to promote healthy sperm volume and good sperm mobility.*

*CLAIMS BASED ON TRADITIONAL HOMEOPATHIC PRACTICE, NOT ACCEPTED MEDICAL EVIDENCE, NOT FDA EVALUATED.

This product is not intended to diagnose, treat, cure, or prevent any disease.

Uses

Temporarily supports your body when dealing with male fertility concerns due to abnormal semen and low or absent sperm production. It also temporarily supports reproductive health and regular male hormone production to promote healthy sperm volume and good sperm mobility.*

*CLAIMS BASED ON TRADITIONAL HOMEOPATHIC PRACTICE, NOT ACCEPTED MEDICAL EVIDENCE, NOT FDA EVALUATED.

This product is not intended to diagnose, treat, cure, or prevent any disease.

KEEP OUT OF REACH OF CHILDREN

Warnings and Storage:

Ask a professional before use if pregnant or breastfeeding or if you have severe symptoms. Keep away from children. If you have a reaction to this product that is not positive, discontinue use. Store in a cool and dry place.

Warnings and Storage:

Ask a professional before use if pregnant or breastfeeding or if you have severe symptoms. Keep away from children. If you have a reaction to this product that is not positive, discontinue use. Store in a cool and dry place.

*CLAIMS BASED ON TRADITIONAL HOMEOPATHIC PRACTICE, NOT ACCEPTED MEDICAL EVIDENCE, NOT FDA EVALUATED.

This product is not intended to diagnose, treat, cure, or prevent any disease.

Entire package label